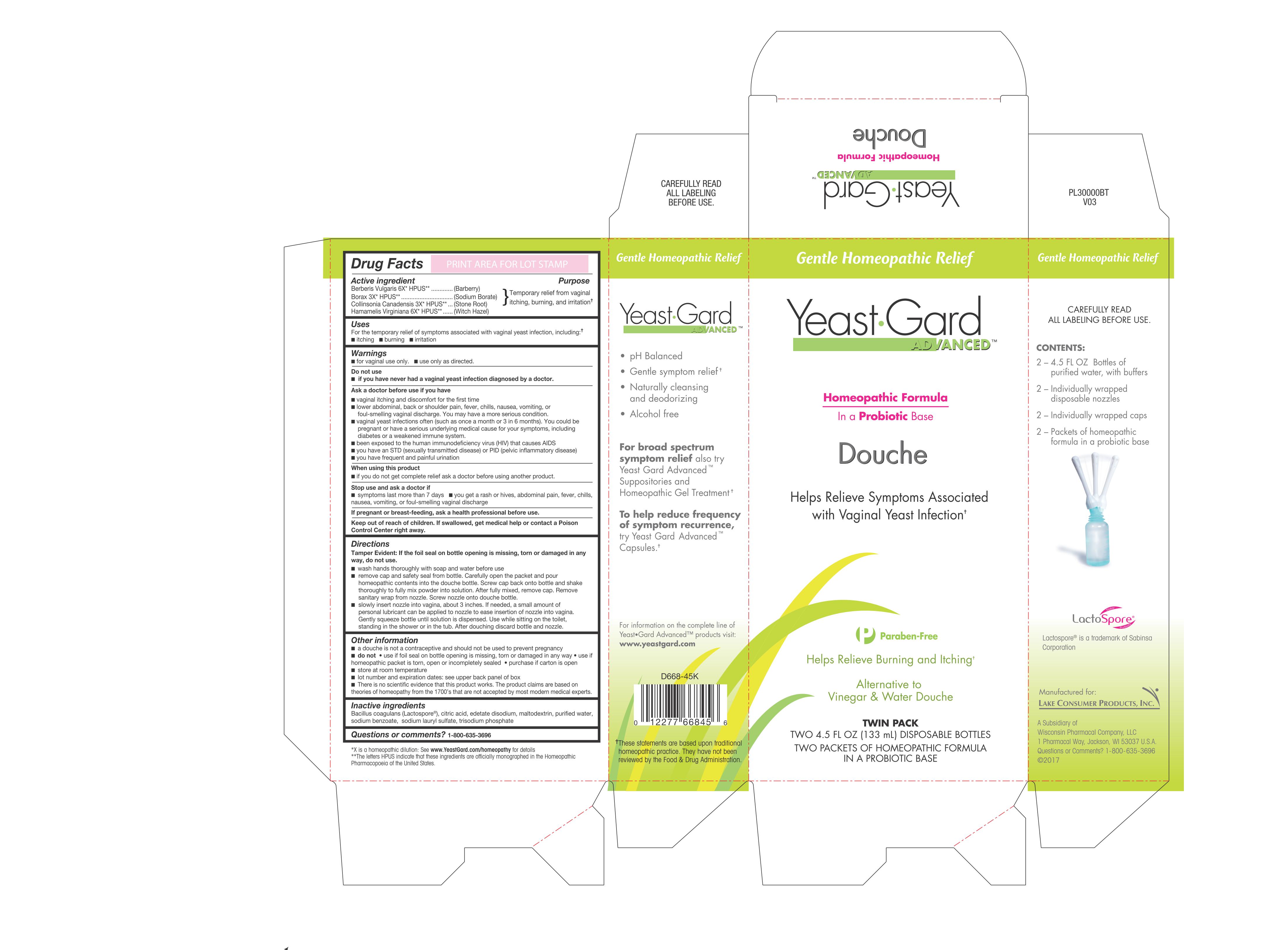 DRUG LABEL: Yeast Gard Advanced
NDC: 68093-0668 | Form: DOUCHE
Manufacturer: Wisconsin Pharmacal Company
Category: homeopathic | Type: HUMAN OTC DRUG LABEL
Date: 20181206

ACTIVE INGREDIENTS: HAMAMELIS VIRGINIANA ROOT BARK/STEM BARK 6 [hp_X]/1 g; BERBERIS VULGARIS ROOT BARK 6 [hp_X]/1 g; SODIUM BORATE 3 [hp_X]/1 g; COLLINSONIA CANADENSIS ROOT 3 [hp_X]/1 g
INACTIVE INGREDIENTS: SODIUM BENZOATE; SODIUM LAURYL SULFATE; BACILLUS COAGULANS; EDETATE DISODIUM; MALTODEXTRIN; CITRIC ACID MONOHYDRATE; WATER; SODIUM PHOSPHATE, TRIBASIC, ANHYDROUS

Active Ingredients

Borax 3X HPUS
Collinsonia Canadensis 3X HPUS
Berberis Vulgaris 6X HPUS
Hamamelis Virginiana 6X HPUS

Purpose

Temporary relief from vaginal itching, burning and irritation

Uses

Uses For the temporary relief of symptoms associated with vagianl yeast infection, including:

- itching
- burning
- irritation

Warnings

- Use only as directed
- For vaginal use only

Ask a doctor before use if you have

- Vaginal itching and discomfort for the first time
- Lower abdominal, back or shoulder pain, fever, chills, nausea, vomiting, or foul-smelling vaginal discharge. You may have a serious condition.
- Vaginal yeast infections often (such as once a month or 3 in 6 months). You could be pregnant or have a serious underlying medical cause for you symptoms, including diabetes or a weakened immune system.
- Been exposed to the human immunodeficiency virus (HIV) that causes AIDS
- You have an STD (sexually transmitted disease) or PID (Pelvic inflammatory disease)
- You have frequent and painful urination

Stop use and ask a doctor if:

- Symptoms last more than 7 days
- You get a rash or hives, abdominal pain, fever, chills, nausea, vomiting, or foul-smelling vagina.

PREGNANCY OR BREAST FEEDING

If pregnant or breast-feeding, ask a health professional before use.

Keep out of reach of children. If swallowed, get medial help or contact a Poison Control Center right away

Do not use

- if you have never had a vaginal yeast infection diagnosed by a doctor

When using this product

- if you do not get complete relief ask a doctor before using another product

Directions

Tamper Evident: If the foil seal on bottle opening is missing, torn or damaged in any way, do not use.

- Wash hands thoroughly with soap and water before and after use
- remove cap and safety seal from bottle. Carefully open teh packet and pour homeopathic contents into the douche bottle. Screw cap back onto bottle and shake thoroughly to fully mix powder into solution. After fully mixed, remove cap. Remove sanitary wrap from nozzle. Screw nozzle onto douche bottle.
- Slowly insert nozzle into vagina about 3 inches. If needed, a small amount of personal lubricant can be applied to nozzle to ease insertion of nozzle into vagina. Gently squeeze bottle until solution is dispensed. Use while sittion on the toilet, standing in the shower or in the tub. After douching discard bottle and nozzle.

Other information

- a douche is not a contraceptive and should not be used to prevent pregnancy
- do not use if foil seal on bottle opening is missing, torn damaged in any way. use if homeopathic packet is torn, open or incompletely sealed. purchase if carton is open
- Store at room temperature
- Lot number and expiration date: see upper back panel of box
- There is no scientific evidence that this product works. Ther product claims are based on theories of homeopathy from the 1700's that are not accepted by most modern medical experts.

Inactive ingredients

Bacillus coagulans, citric acid, edetate disodium, maltodextrin, purified water, sodium benzoate, sodium lauryl sulfate, trisodium phosphate

Questions or commetns? 1-800-635-3696